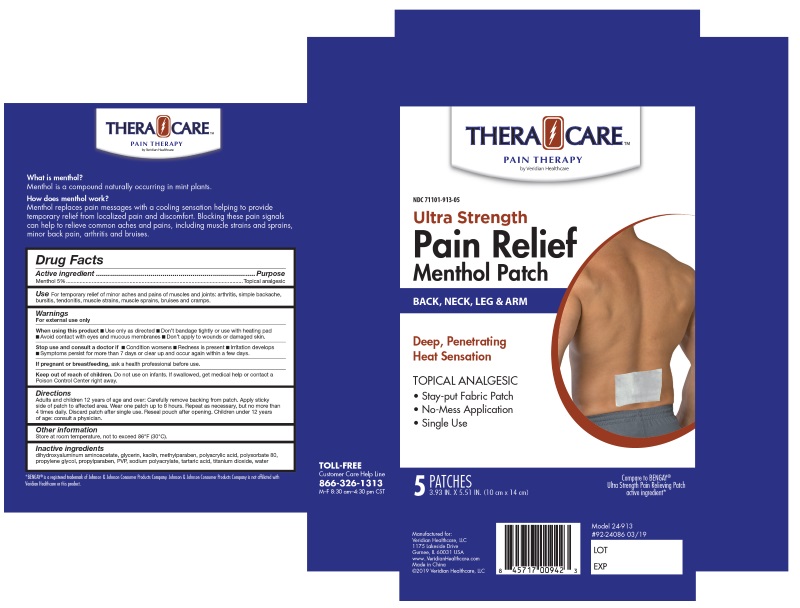 DRUG LABEL: Thera Care Pain Relief Menthol Patchs
NDC: 71101-913 | Form: PATCH
Manufacturer: Veridian Healthcare
Category: otc | Type: HUMAN OTC DRUG LABEL
Date: 20251230

ACTIVE INGREDIENTS: MENTHOL 5 g/100 g
INACTIVE INGREDIENTS: DIHYDROXYALUMINUM AMINOACETATE; GLYCERIN; KAOLIN; METHYLPARABEN; POLYACRYLIC ACID (250000 MW); POLYSORBATE 80; PROPYLENE GLYCOL; PROPYLPARABEN; POVIDONE, UNSPECIFIED; SODIUM POLYACRYLATE (2500000 MW); TARTARIC ACID; TITANIUM DIOXIDE; WATER

Thera Care Pain Relief Menthol Patches

ACTIVE INGREDIENT

Active Ingredient ...............................................................................................Purpose
Menthol 5%...............................................................................................Topical Analgesic

INACTIVE INGREDIENT

dihydroxyaluminum aminoacetate, glycerin, kaolin, methylparaben, polyacrylic acid, polysorbate 80, propylene glycol, propylparaben, PVP, sodium polyacrylate, tartaric acid, titanium dioxide, water

KEEP OUT OF REACH OF CHILDREN

If swallowed, get medical help or contact a Poison Control

INDICATIONS & USAGE

Temporarily relieves minor pain associated with: ■ arthritis ■ simple backache ■ bursitis ■ tendonitis
■ muscle strains ■ muscle sprains ■ bruises ■ cramps

WARNINGS

For External Use Only.

DOSAGE & ADMINISTRATION

Adults and children over 12 years: Carefully remove backing from patch. Apply sticky side of patch to affected area.

Wear one patch up to 8 hours. Repeat as necessary, but no more than 4 times daily. Reseal pouch after opening.

Children 12 years or younger: Consult a physician.

PURPOSE

Topical Analgesic

When using this product

Use only as directed ■ Don’t bandage tightly or use with heating pad
■ Avoid contact with eyes and mucous membranes ■ Don’t apply to wounds or damaged skin.

Stop use and ask a doctor

If condition worsens ■ If redness is present ■ If irritation develops
■ If symptoms persist for more than 7 days or clear up and occur again within a few days.

If pregnant or breastfeeding

ask a health professional before use.

PACKAGE LABEL

Manufactured For
Veridian Healthcare, LLC
Gurnee, IL 60031

TOLL-FREE CUSTOMER CARE HELP LINE Mon–Fri, 8:30 am–4:30 pm CST 866-326-1313